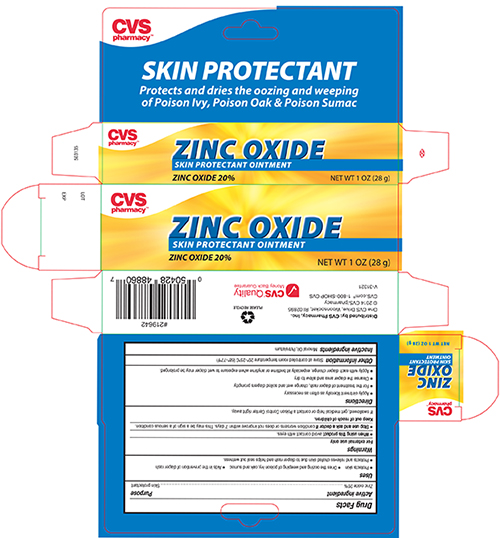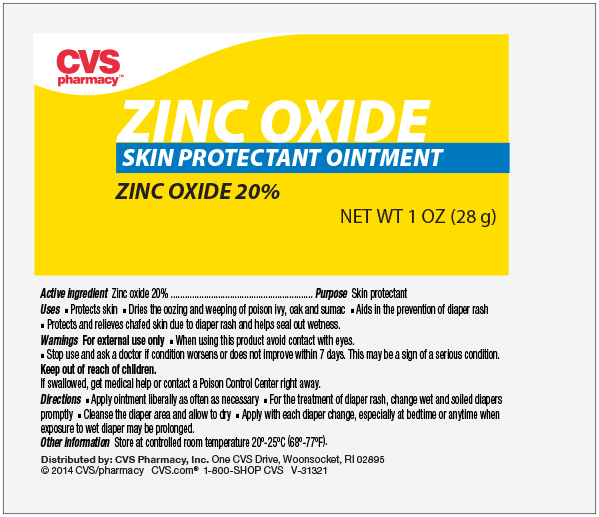 DRUG LABEL: CVS Zinc Oxide
NDC: 69842-065 | Form: OINTMENT
Manufacturer: CVS Health
Category: otc | Type: HUMAN OTC DRUG LABEL
Date: 20241111

ACTIVE INGREDIENTS: ZINC OXIDE 200 mg/1 g
INACTIVE INGREDIENTS: MINERAL OIL; PETROLATUM

Drug Facts

Active ingredient

Zinc oxide 20%

Purpose

Skin Protectant

Uses

- helps treat and prevent diaper rash. Protects chafed skin due to diaper rash and helps seal out wetness.
- dries the oozing and weeping of poison ivy, poison oak and poison sumac.

Warnings

For external use only

When using this product, avoid contact with the eyes

Stop use and ask a doctor if condition worsens or does not improve within 7 days

Keep out of reach of children. If swallowed, get medical help or contact a poison control center right away.

Directions

- apply liberally as often as necessary

For diaper rash:

- change wet or soiled diapers promptly
- cleanse the diaper area and allow to dry
- apply ointment liberally, as often as necessary, with each diaper change and especially at bedtime or anytime when exposure to wet diapers may be prolonged

Inactive ingredients

mineral oil, petrolatum

Questions or comments?

Store at room temperature 20° - 25°C (68° - 77°F).

Zinc Oxide Tube 1oz

CVS Pharmacy

ZINC OXIDE

Skin Protectant Ointment

ZINC OXIDE 20% NET WT 1 oz (28g)

CVS Zinc Oxide 1 oz Carton

CVS Pharmacy

Zinc Oxide

Skin Protectant Ointment

Zinc Oxide 20% NET WT 1 oz (28g)